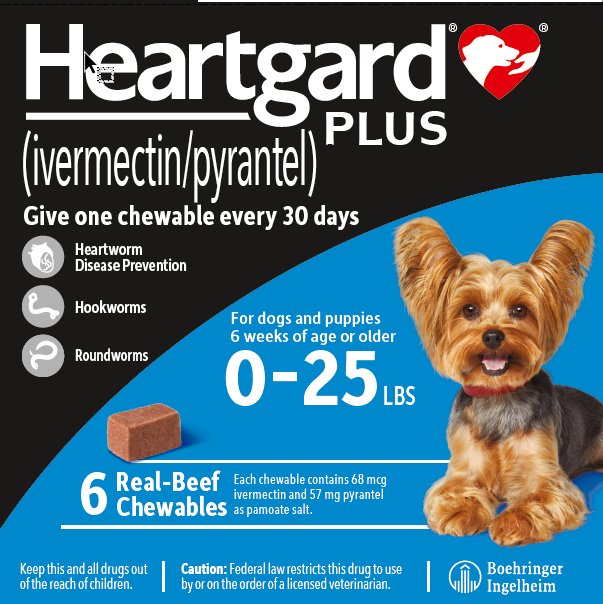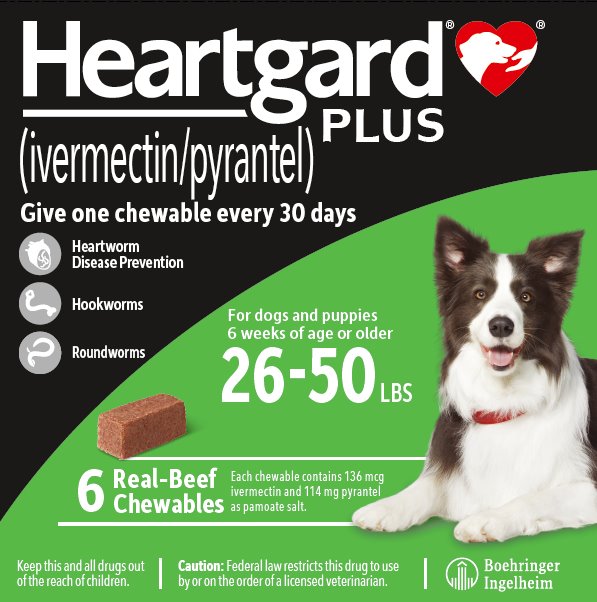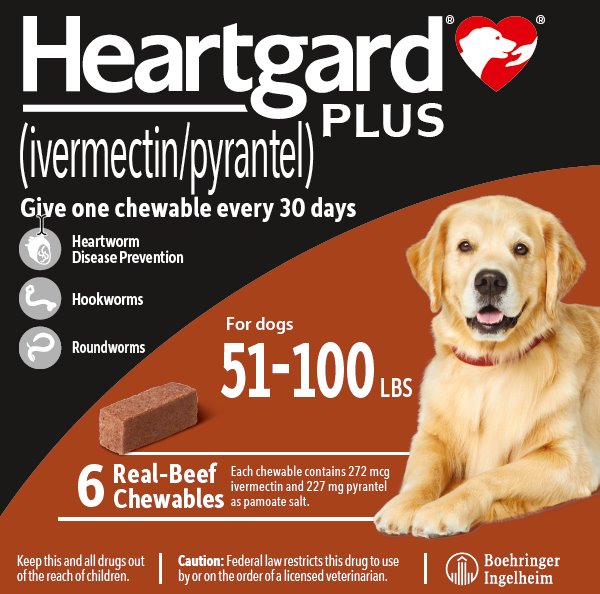 DRUG LABEL: HEARTGARD
NDC: 0010-4012 | Form: TABLET, CHEWABLE
Manufacturer: Boehringer Ingelheim Animal Health USA Inc.
Category: animal | Type: PRESCRIPTION ANIMAL DRUG LABEL
Date: 20231019

ACTIVE INGREDIENTS: ivermectin 68 ug/1 1; pyrantel pamoate 57 mg/1 1

HEARTGARD® PLUS
(ivermectin/pyrantel)

Approved by FDA under NADA # 140-971

Chewables

Caution:

Federal law restricts this drug to use by or on the order of a licensed veterinarian.

Indications:

For use in dogs to prevent canine heartworm disease by eliminating the tissue stage of heartworm larvae (Dirofilaria immitis) for a month (30 days) after infection and for the treatment and control of roundworms (Toxocara canis, Toxascaris leonina) and hookworms (Ancylostoma caninum, Uncinaria stenocephala, Ancylostoma braziliense).

Dosage:

HEARTGARD® PLUS should be administered orally at monthly intervals at the recommended minimum dose level of 6 mcg of ivermectin per kilogram (2.72 mcg/lb) and 5 mg of pyrantel (as pamoate salt) per kg (2.27 mg/lb) of body weight. The recommended dosing schedule for prevention of canine heartworm disease and for the treatment and control of roundworms and hookworms is as follows:

Dog Weight | Chewables Per Month | Ivermectin Content | Pyrantel Content | Color Coding on Foil Backing and Carton
0 - 25 lbs | 1 | 68 mcg | 57 mg | Blue
26 - 50 lbs | 1 | 136 mcg | 114 mg | Green
51 - 100 lbs | 1 | 272 mcg | 227 mg | Brown
HEARTGARD® PLUS is recommended for dogs 6 weeks of age and older.
For dogs over 100 lbs use the appropriate combination of these chewables.

Administration:

Remove only one chewable at a time from the foil-backed blister card. Return the card with the remaining chewables to its box to protect the product from light.

Because most dogs find HEARTGARD® PLUS palatable, the product can be offered to the dog by hand. To avoid the risk of choking or intestinal obstruction, the chewable should be administered in a manner that encourages the dog to chew, rather than to swallow without chewing (see Precautions and Post-Approval Experience). Alternatively, it may be added intact to a small amount of dog food to encourage chewing, but care should be taken to ensure that the dog consumes the complete dose at one time.

Treated animals should be observed for a few minutes after administration to ensure that part of the dose is not lost or rejected. If it is suspected that any of the dose has been lost, redosing is recommended.

HEARTGARD® PLUS should be given at monthly intervals during the period of the year when mosquitoes (vectors), potentially carrying infective heartworm larvae, are active. The initial dose must be given within a month (30 days) after the dog's first exposure to mosquitoes. The final dose must be given within a month (30 days) after the dog's last exposure to mosquitoes.

When replacing another heartworm preventive product in a heartworm disease preventive program, the first dose of HEARTGARD® PLUS must be given within a month (30 days) of the last dose of the former medication.

If the interval between doses exceeds a month (30 days), the efficacy of ivermectin can be reduced. Therefore, for optimal performance, the chewable must be given once a month on or about the same day of the month. If treatment is delayed, whether by a few days or many, immediate treatment with HEARTGARD® PLUS and resumption of the recommended dosing regimen minimizes the opportunity for the development of adult heartworms.

Monthly treatment with HEARTGARD® PLUS also provides effective treatment and control of roundworms (T. canis, T. leonina) and hookworms (A. caninum, U. stenocephala, A. braziliense). Clients should be advised of measures to be taken to prevent reinfection with intestinal parasites.

Efficacy:

HEARTGARD® PLUS (ivermectin/pyrantel) Chewables, given orally using the recommended dose and regimen, are effective against the tissue larval stage of D. immitis for a month (30 days) after infection and, as a result, prevent the development of the adult stage. HEARTGARD® PLUS Chewables are also effective against canine roundworms (T. canis, T. leonina) and hookworms (A. caninum, U. stenocephala, A. braziliense).

Acceptability:

In acceptability and field trials, HEARTGARD® PLUS was shown to be an acceptable oral dosage form that was consumed at first offering by the majority of dogs.

Precautions:

All dogs should be tested for existing heartworm infection before starting treatment with HEARTGARD® PLUS which is not effective against adult D. immitis. Infected dogs must be treated to remove adult heartworms and microfilariae before initiating a program with HEARTGARD® PLUS.

While some microfilariae may be killed by the ivermectin in HEARTGARD® PLUS at the recommended dose level, HEARTGARD® PLUS is not effective for microfilariae clearance. A mild hypersensitivity-type reaction, presumably due to dead or dying microfilariae and particularly involving a transient diarrhea, has been observed in clinical trials with ivermectin alone after treatment of some dogs that have circulating microfilariae.

Choking or intestinal obstruction has been reported after dosing with HEARTGARD® PLUS. For dogs that normally swallow treats whole, chewables may be broken into pieces (see Post-Approval Experience).

STORAGE AND HANDLING

Keep this and all drugs out of the reach of children. In case of ingestion by humans, clients should be advised to contact a physician immediately. Physicians may contact a Poison Control Center for advice concerning cases of ingestion by humans.

Keep HEARTGARD® PLUS in a secure location out of reach of dogs, cats, and other animals to prevent accidental ingestion or overdose.

Adverse Reactions:

In clinical field trials with HEARTGARD® PLUS, vomiting or diarrhea within 24 hours of dosing was observed (1.1% of administered doses).

Post-Approval Experience (2022): The following adverse events are based on post-approval adverse drug experience reporting for HEARTGARD® PLUS. Not all adverse events are reported to FDA/CVM. It is not always possible to reliably estimate the adverse event frequency or establish a causal relationship to product exposure using these data.

The following adverse events reported in dogs are listed in decreasing order of reporting frequency:

Vomiting, diarrhea, lethargy, anorexia, seizures, ataxia, muscle tremors, hypersalivation, pruritus.

In some cases, choking or intestinal obstruction has been reported after administration of HEARTGARD® PLUS.

Contact Information: To report suspected adverse drug events, for technical assistance, or to obtain a copy of the Safety Data Sheet (SDS), contact Boehringer Ingelheim Animal Health USA Inc. at 1-888-637-4251. For additional information about adverse drug experience reporting for animal drugs, contact FDA at 1-888-FDA-VETS, or www.fda.gov/reportanimalae.

Safety:

HEARTGARD® PLUS has been shown to be bioequivalent to HEARTGARD®, with respect to the bioavailability of ivermectin. The dose regimens of HEARTGARD® PLUS and HEARTGARD® are the same with regard to ivermectin (6 mcg/kg). Studies with ivermectin indicate that certain dogs of the Collie breed are more sensitive to the effects of ivermectin administered at elevated dose levels (more than 16 times the target use level) than dogs of other breeds. At elevated doses, sensitive dogs showed adverse reactions which included mydriasis, depression, ataxia, tremors, drooling, paresis, recumbency, excitability, stupor, coma and death. HEARTGARD® demonstrated no signs of toxicity at 10 times the recommended dose (60 mcg/kg) in sensitive Collies. Results of these trials and bioequivalency studies, support the safety of HEARTGARD® products in dogs, including Collies, when used as recommended.

HEARTGARD® PLUS has shown a wide margin of safety at the recommended dose level in dogs, including pregnant or breeding bitches, stud dogs and puppies aged 6 or more weeks. In clinical trials, many commonly used flea collars, dips, shampoos, anthelmintics, antibiotics, vaccines and steroid preparations have been administered with HEARTGARD® PLUS in a heartworm disease preventive program.

In one trial, where some pups had parvovirus, there was a marginal reduction in efficacy against intestinal nematodes, possibly due to a change in intestinal transit time.

How Supplied:

HEARTGARD® PLUS is available in three dosage strengths (see Dosage) for dogs of different weights. Each strength comes in convenient cartons of 1, 6 and 12 chewables.

Storage Information:

Store between 68° F - 77° F (20° - 25° C). Excursions between 59° F - 86° F (15° - 30° C) are permitted. Protect product from light.

Marketed by:

Boehringer Ingelheim Animal Health USA Inc.
Duluth, GA 30096

HEARTGARD®and the Dog & Hand logo® are registered trademarks of Boehringer Ingelheim Animal Health USA Inc.

©2023 Boehringer Ingelheim Animal Health USA Inc. All rights reserved.

Rev. 03-2023
151749-005; 162813-003; (1050-1999-07)